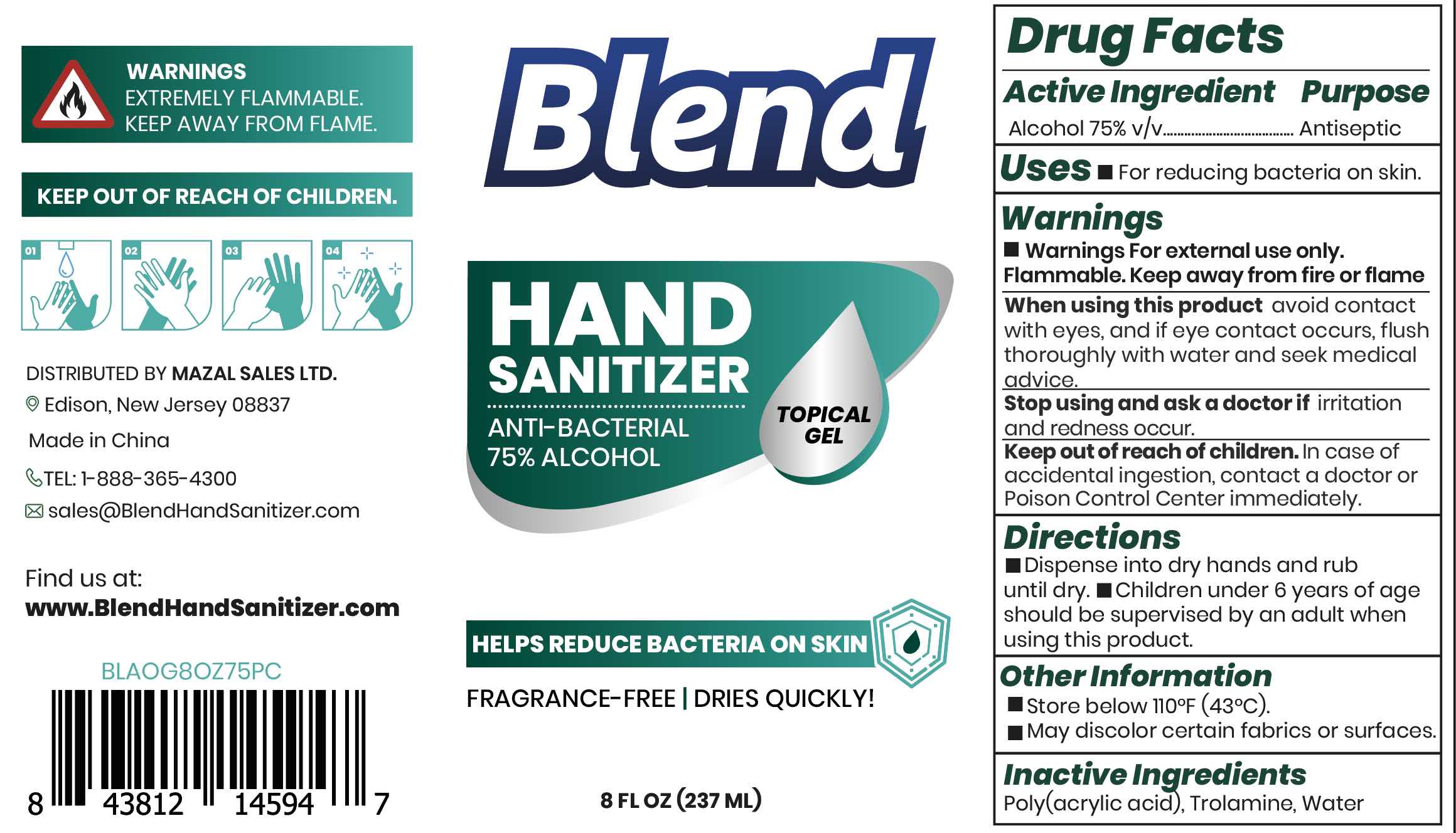 DRUG LABEL: Blend Hand Sanitizer
NDC: 80512-001 | Form: GEL
Manufacturer: MAZAL SALES LTD.
Category: otc | Type: HUMAN OTC DRUG LABEL
Date: 20201023

ACTIVE INGREDIENTS: ALCOHOL 75 mL/100 mL
INACTIVE INGREDIENTS: POLYACRYLIC ACID (250000 MW); WATER; TROLAMINE

Mazal AO Blend Sanitizer Gel 75

Active Ingredient

Alcohol 75%v/v

Purpose

Antiseptic

Uses

■ For reducing bacteria on the skin.

Warnings

■ Warnings For external use only. Flammable. Keep away from heat or flame

When using this product

avoid contact with eyes, and if eye contact occurs, flush thoroughly with water and seek medical advice

Stop use and ask a doctor if

irritation or rash occurs. These may be the signs of a serious condition.

Keep out of reach of children

In case of accidentail ingestion, contact a doctor or Poison Control Center immediately.

Directions

■ Dispense into dry hands and rub until dry. ■ Children under 6 years of age should be supervised by an adult when using this product.

Other information

■Store below 110ºF (43ºC)

■ May discolor certain fabrics or surfaces.

Inactive ingredients

Poly(acrylic acid), Trolamine, Water